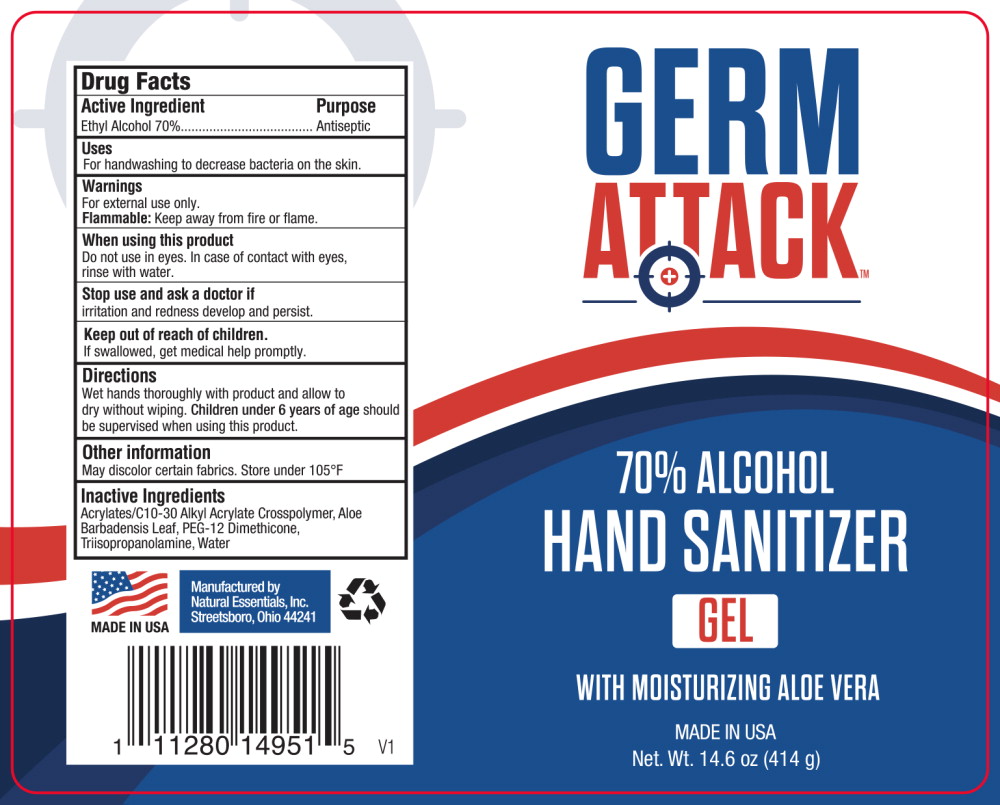 DRUG LABEL: Germ Attack Hand Sanitizer
NDC: 66902-943 | Form: GEL
Manufacturer: Natural Essentials, Inc.
Category: otc | Type: HUMAN OTC DRUG LABEL
Date: 20241004

ACTIVE INGREDIENTS: ALCOHOL 0.7 mL/1 mL
INACTIVE INGREDIENTS: CARBOMER INTERPOLYMER TYPE A (ALLYL SUCROSE CROSSLINKED); ALOE VERA LEAF; POLYETHYLENE GLYCOL 300; PEG-12 DIMETHICONE (300 CST); TRIISOPROPANOLAMINE; WATER

Drug Facts

Active Ingredient

Ethyl Alcohol 70%

Purpose

Antiseptic

Uses

For handwashing to decrease bacteria on the skin.

Warnings

For external use only.

Flammable:Keep away from fire or flame.

When using this product

Do not use in eyes. In case of contact with eyes, rinse with water.

Stop use and ask a doctor if

irritation and redness develop and persist.

Keep out of reach of children.

If swallowed, get medical help promptly.

Directions

Wet hands thoroughly with product and allow to dry without wiping. Children under 6 years of ageshould be supervised when using this product.

Other information

May discolor certain fabrics. Store under 105°F

Inactive Ingredients

Acrylates/C10-30 Alkyl Acrylate Crosspolymer, Aloe Barbadensis Leaf, PEG-12 Dimethicone, Triisopropanolamine, Water

Principal Display Panel – 414 g Bottle Label

GERM

ATTACK™

70% ALCOHOL

HAND SANITIZER
GEL

WITH MOISTURIZING ALOE VERA

MADE IN USA

Net. Wt. 14.6 oz (414 g)